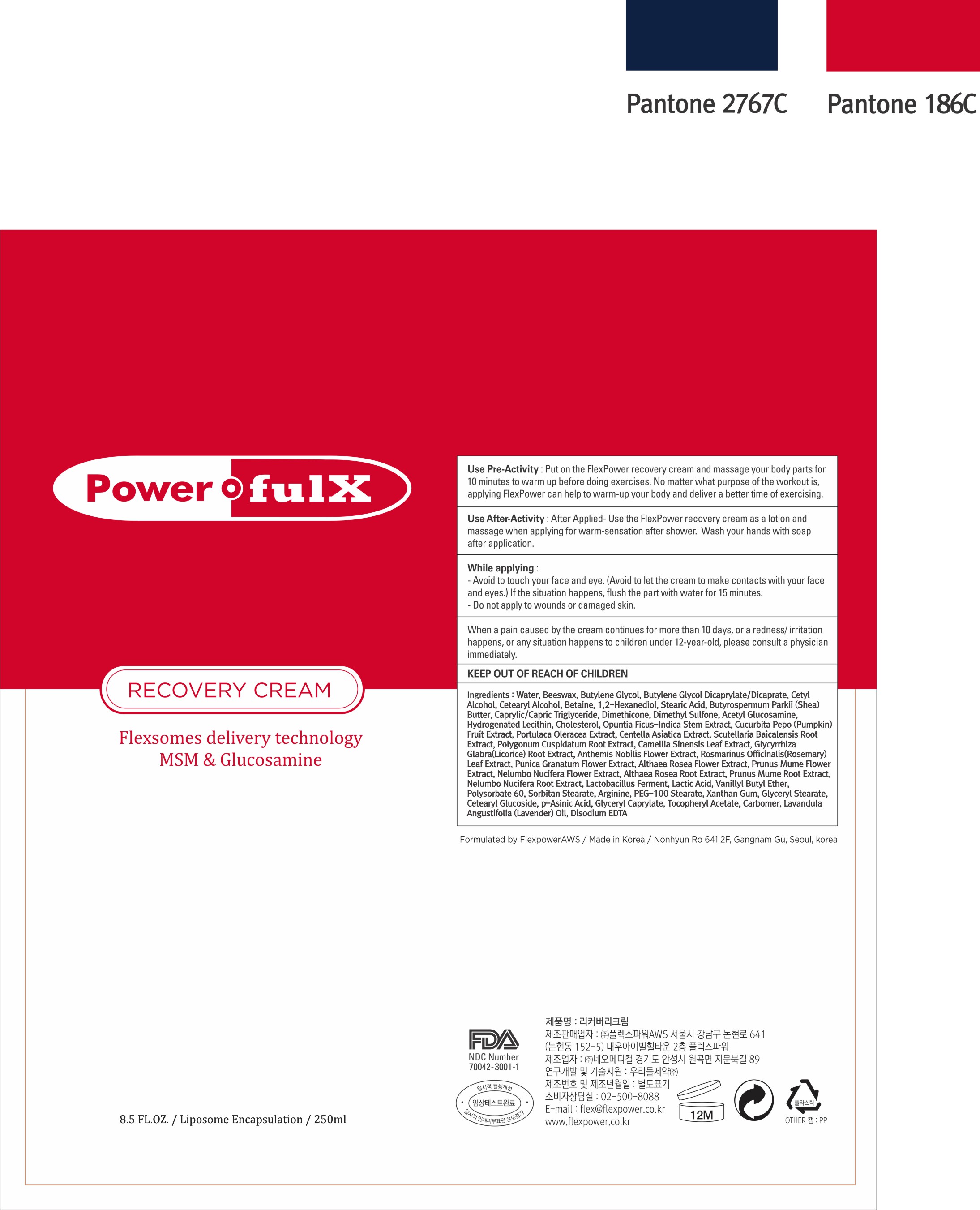 DRUG LABEL: RECOVERY
NDC: 70042-0002 | Form: CREAM
Manufacturer: Powerful X
Category: otc | Type: HUMAN OTC DRUG LABEL
Date: 20210107

ACTIVE INGREDIENTS: STEARIC ACID 1.5 g/100 mL
INACTIVE INGREDIENTS: WATER; BUTYLENE GLYCOL

Drug Facts

ACTIVE INGREDIENT

Stearic Acid

INACTIVE INGREDIENT

Water, Butylene Glycol, etc

PURPOSE

Warm up pre/after-execise and after shower

keep out of reach of the children

WARNINGS

- Avoid to touch your face and eye. (Avoid to let the cream to make contacts with your face and eyes.) If the situcation happens, flush the part with water for 15 minutes.
- Do not apply to wounds or damaged skin.
- When a pain caused by the cream continues for more than 10 days, or a redness/irritation happens, or any situation happens to children under 12-year-old, please consult a physician immediately.

DOSAGE AND ADMINISTRATION

for external use only

INDICATIONS AND USAGE

- Use Pre- Activity: Put on the FlexPower recovery cream and massage your body parts for 10 minutes to warm up before doing exercises. No matter what purpose of the workout is, applyting FlexPower can help to warm-up your body and deliver a better time of exercising.
- Use After-Activty: After Applied- Use the FlexPower recovery cream as a lotion and massage when applying for warm-sensation after shower. Wash your hand with soap after application.